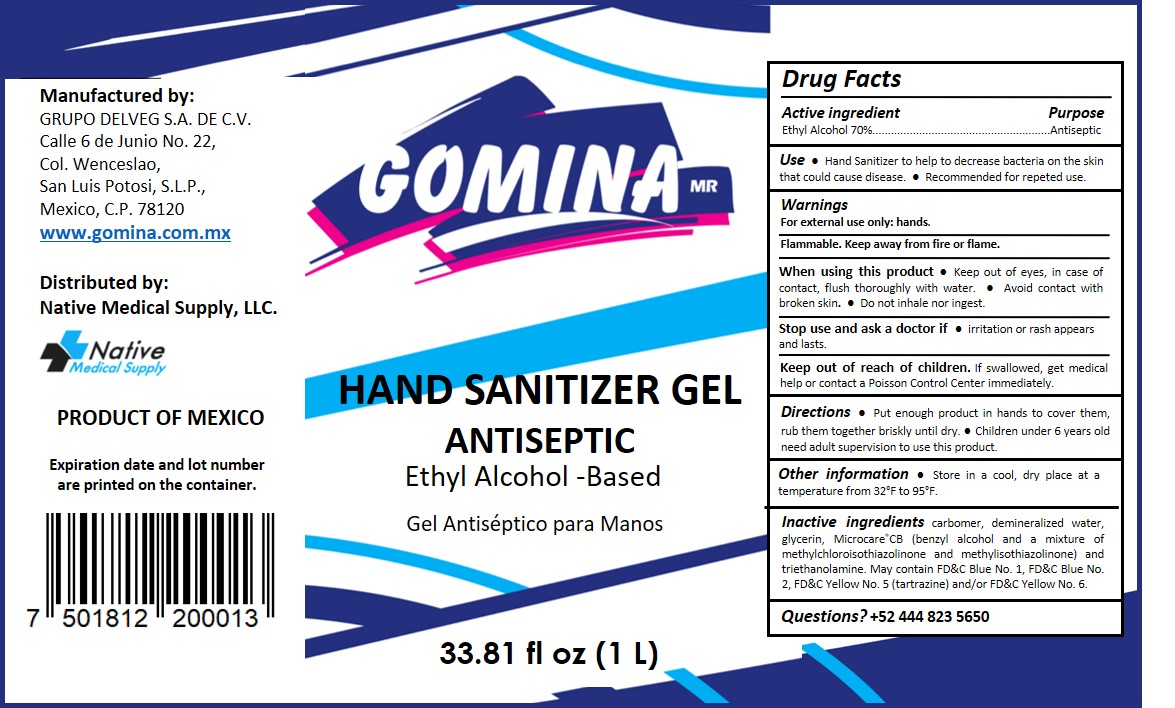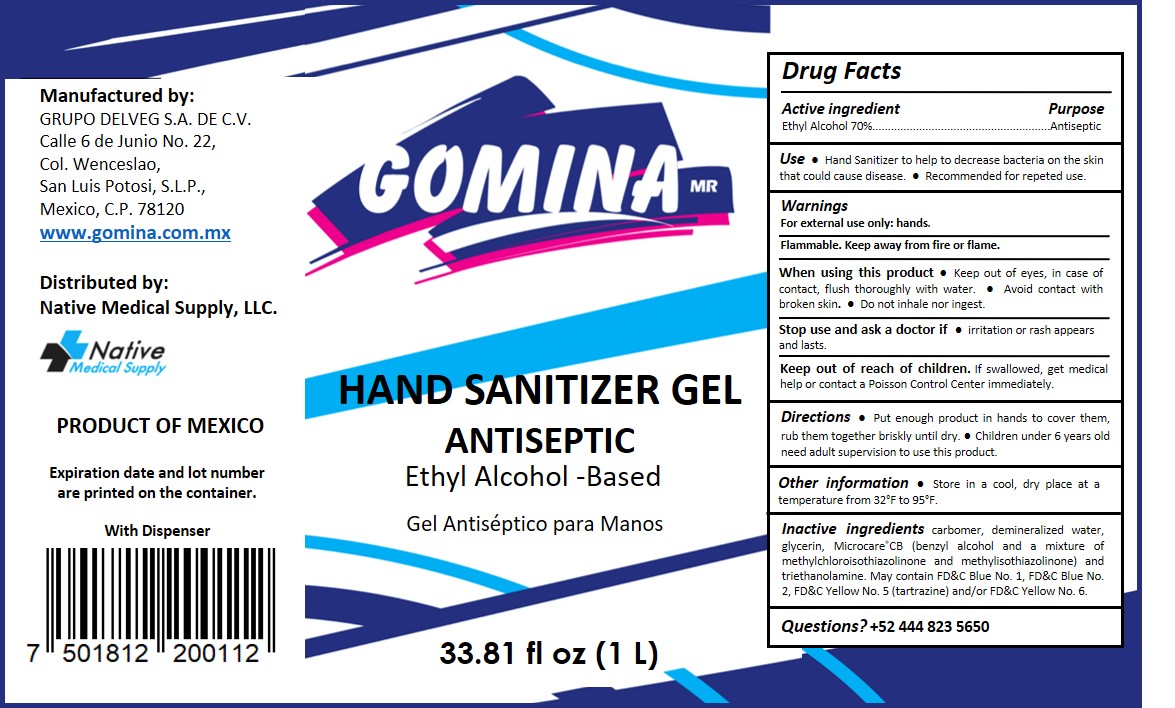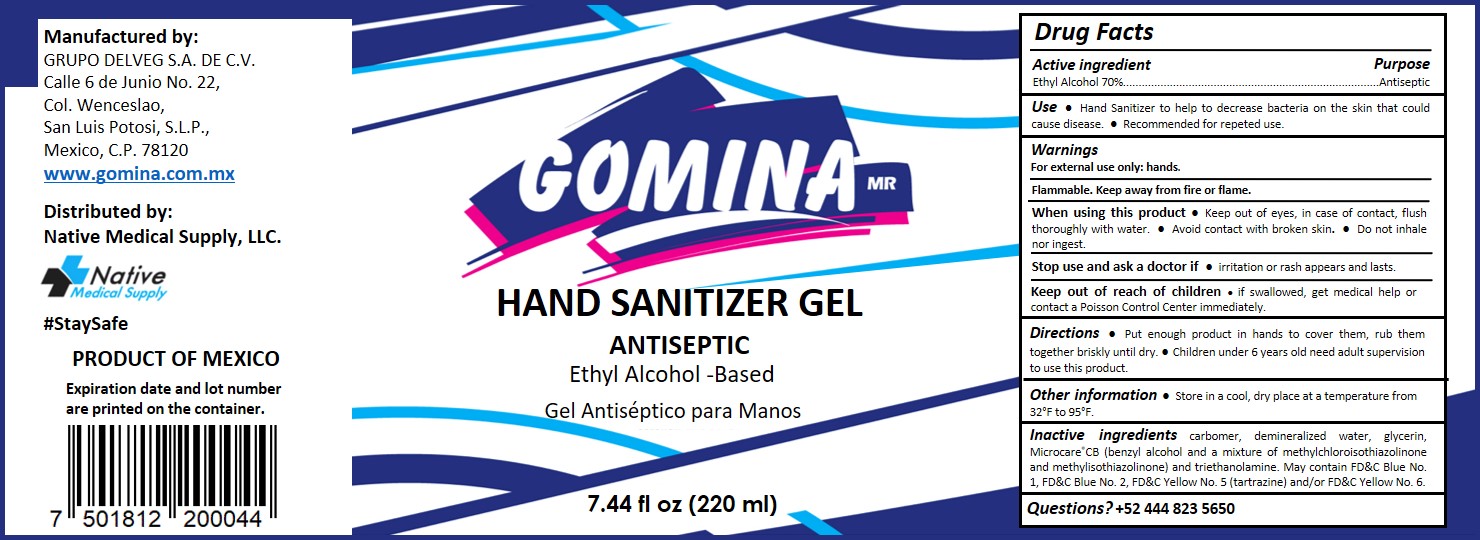 DRUG LABEL: Hand Sanitizer
NDC: 79008-002 | Form: GEL
Manufacturer: Grupo Delveg, S.A. de C.V.
Category: otc | Type: HUMAN OTC DRUG LABEL
Date: 20201002

ACTIVE INGREDIENTS: ALCOHOL 70 mL/100 mL
INACTIVE INGREDIENTS: FD&C BLUE NO. 2; FD&C YELLOW NO. 5; FD&C YELLOW NO. 6; FD&C BLUE NO. 1; GLYCERIN; WATER; TROLAMINE; CARBOMER 940; BENZYL ALCOHOL; METHYLCHLOROISOTHIAZOLINONE/METHYLISOTHIAZOLINONE MIXTURE

Gomina Hand Sanitizer

Active Ingredient(s)

Ethyl Alcohol 70% v/v. Purpose: Antiseptic

Purpose

Antiseptic, Hand Sanitizer

Use

Hand Sanitizer to help to decrease bacteria on the skin that could cause disease. Recommended for repeted use.

Warnings

For external use only: hands. Flammable. Keep away from fire or flame.

WHEN USING

Keep out of eyes, in case of contact, flush thoroughly with water. Avoid contact with broken skin. Do not inhale nor ingest.

Stop use and ask a doctor if irritation or rash appears and lasts.

Keep out of reach of children if swallowed, get medical help or contact a Poisson Control Center immediately.

Directions

- Put enough product in hands to cover them, rub them together briskly until dry.
- Children under 6 years old need adult supervision to use this product.

Other information

- Store in a cool, dry place at a temperature from 32°F to 95°F.

Inactive ingredients

carbomer, demineralized water, glycerin, Microcare®CB (benzyl alcohol and a mixture of methylchloroisothiazolinone and methylisothiazolinone) and triethanolamine. May contain FD&C Blue No. 1, FD&C Blue No. 2, FD&C Yellow No. 5 (tartrazine) and/or FD&C Yellow No. 6.

Questions? +52 444 823 5650

Label NDC 79008-001

1000 mL NDC: 79008-001-01

Label NDC: 79008-001-02

220 mL NDC: 79008-001-02

Label NDC 79008-001-03

1000 mL NDC: 79008-001-03

Bottle w/dispenser

Label NDC 79008-002-01

1000 mL NDC: 79008-002-01

Label NDC: 79008-002-02

220 mL NDC: 79008-002-02

Label NDC 79008-002-03

1000 mL NDC: 79008-002-03

Bottle w/dispenser

Label NDC 79008-003-01

1000 mL NDC: 79008-003-01

Label NDC: 79008-003-02

220 mL NDC: 79008-003-02

Label NDC 79008-003-03

1000 mL NDC: 79008-003-03

Bottle w/dispenser